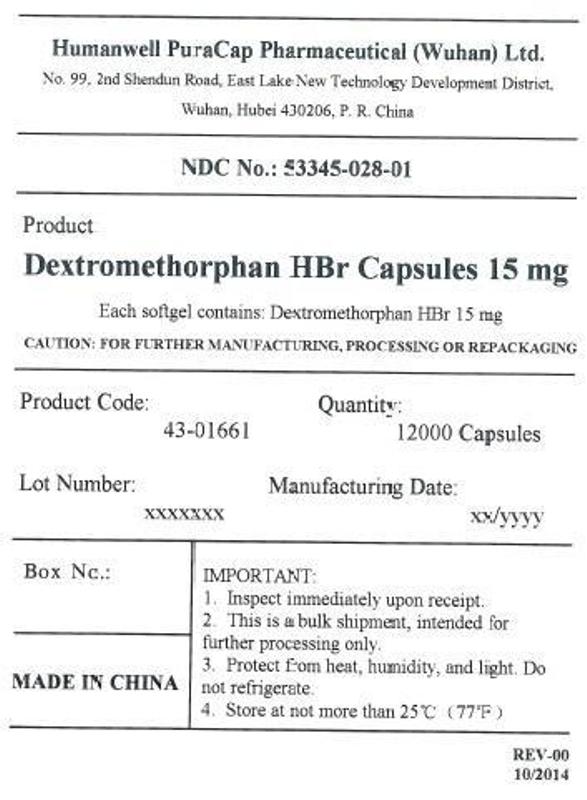 DRUG LABEL: Dextromethorphan HBr 15 mg
NDC: 53345-028 | Form: CAPSULE, LIQUID FILLED
Manufacturer: Humanwell PuraCap Pharmaceuticals (Wuhan) Co., Ltd.
Category: otc | Type: HUMAN OTC DRUG LABEL
Date: 20241125

ACTIVE INGREDIENTS: DEXTROMETHORPHAN HYDROBROMIDE 15 mg/1 1
INACTIVE INGREDIENTS: FD&C RED NO. 40; FD&C BLUE NO. 1; GELATIN; GLYCERIN; POLYETHYLENE GLYCOL 400; POVIDONE; WATER; PROPYLENE GLYCOL; SORBITOL

Dextromethorphan HBr Capsules 15 mg, liquid filled

Active ingredient (in each softgel)

Dextromethorphan HBr, USP 15 mg

Purpose

Cough suppressant

Use

temporarily relieves cough due to minor throat and bronchial irritation as may occur with a cold

Warnings

DO NOT USE

Do not useifyou are now taking a prescription monoamine oxidase inhibitor (MAOI) (certain drugs for depression, psychiatric, or emotional conditions, or Parkinson's disease), or for 2 weeks after stopping the MAOI drug. If you do not know if your prescription drug contains an MAOI, ask a doctor or pharmacist before taking this product.

Ask a doctor before use if the user has

- a cough that occurs with too much phlegm (mucus)
- a cough that lasts or is chronic as occurs with smoking, asthma, or emphysema

Stop use and ask a doctor ifcough lasts for more than 7 days, comes back, or is accompanied by fever, rash, or persistent headache. These could be signs of a serious condition.

PREGNANCY OR BREAST FEEDING

If pregnant or breast-feeding,ask a health professional before use.

Keep out of reach of children.In case of overdose, get medical help or contact a Poison Control Center right away.

Directions

- do not take more than 8 capsules in any 24-hour period
- this adult product is not intended for use in children under 12 years of age

adults and children 12 years of age and over | take 2 capsules every 6 to 8 hours, as needed
children under 12 years of age | do not use

Other information

- store at 20-25°C (68-77°F)
- avoid excessive heat above 40°C (104°F)
- protect from light

Inactive ingredients

FD&C blue #1, FD&C Red #40, gelatin, glycerin, polyethylene glycol, povidone, propylene glycol, purified water, sorbitol special, and white edible ink

Manufactured by:
Humanwell PuraCap Pharmaceutical (Wuhan) Co., Ltd.
Wuhan, Hubei
430206, China

Questions or comments?

Call toll free 1-855-215-8180

PRINCIPAL DISPLAY PANEL - Shipping Label

Dextromethorphan HBr Capsules, 15 mg

Quantity : 12000 Capsules
NDC No. : 53345-028-01

IMPORTANT:

Inspect immediate upon receipt.
This is a bulk shipment intended for further processing only.
Protect from heat, humidity, and light. Do not refrigerate.

CAUTION : "FOR FURTHER MANUFACTURING, PROCESSING OR REPACKING"